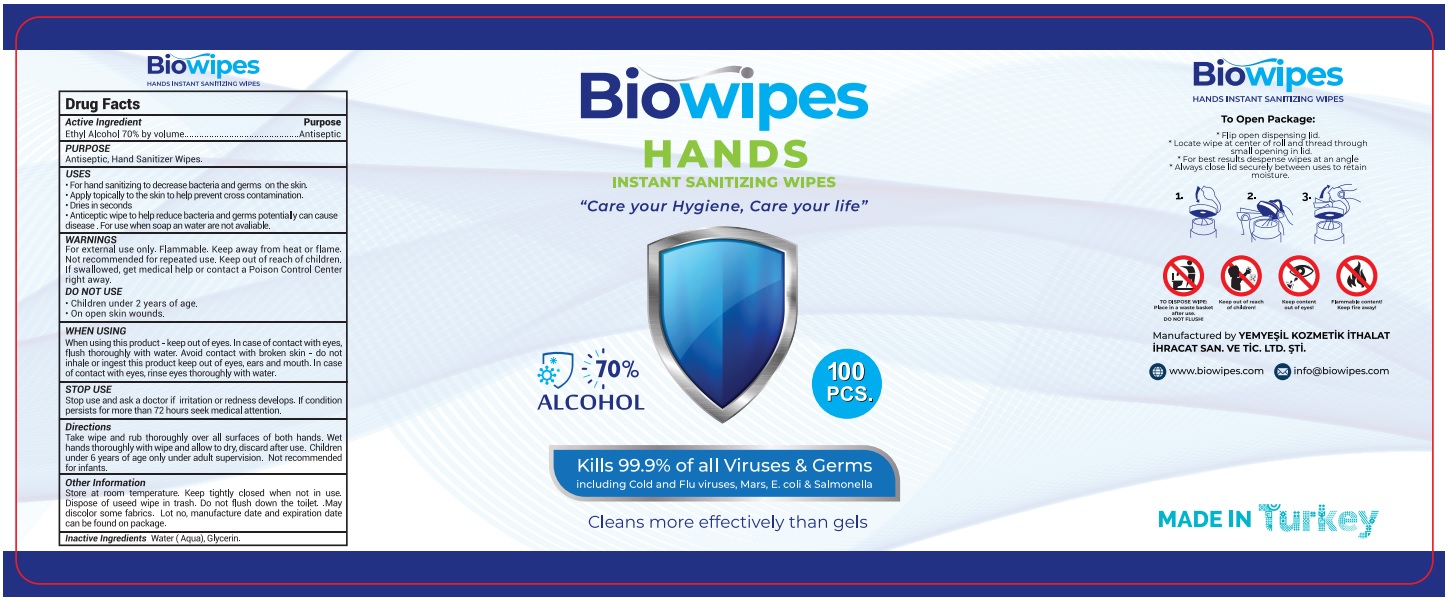 DRUG LABEL: Biowipes Alcohol Wipes
NDC: 81088-101 | Form: CLOTH
Manufacturer: YEMYESIL KOZMETIK ITHALAT IHRACAT SANAYI VE TICARET LIMITED SIRKETI
Category: otc | Type: HUMAN OTC DRUG LABEL
Date: 20201117

ACTIVE INGREDIENTS: ALCOHOL 70 mL/100 1
INACTIVE INGREDIENTS: GLYCERIN; WATER

ACTIVE INGREDIENT

Alcohol 70% v/w

PURPOSE

Antiseptic, Hand sanitizer wipes

INDICATIONS AND USAGE

- For hand sanitizing to decrease bacteria and germs on the skin.

- Apply topically to the skin to help prevent cross contamination.

- Dries in seconds

- Anticeptic wipe to help reduce bacteria and germs potentially can cause disease. For use when soap an water are not available.

WARNINGS

For external use only. Flammable. Keep away from heat or flame. Not recommended for repeated use. Keep out of reach of children. If swallowed, get medical help or contact a Poison Control Center right away.

DO NOT USE

- Children under 2 years of age.

- On open skin wounds.

When using this product - keep out of eyes. In case of contact with eyes, flush thoroughly with water. Avoid contact with broken skin - do not inhale or ingest this product keep out of eyes, ears and mouth. In case of contact with eyes, rinse eyes thoroughly with water.

Stop use and ask a doctor if irritation or redness develops. If condition persists for more than 72 hours seek medical attention.

Keep out of reach of children.

STORAGE AND HANDLING

- Store between 15-30°C (59-86°F).
- Avoid freezing and excessive heat above 40°C (104°F).

INACTIVE INGREDIENT

Water, Glycerin

DOSAGE AND ADMINISTRATION

Use it as needed, after following the usage instructions. For external use only.